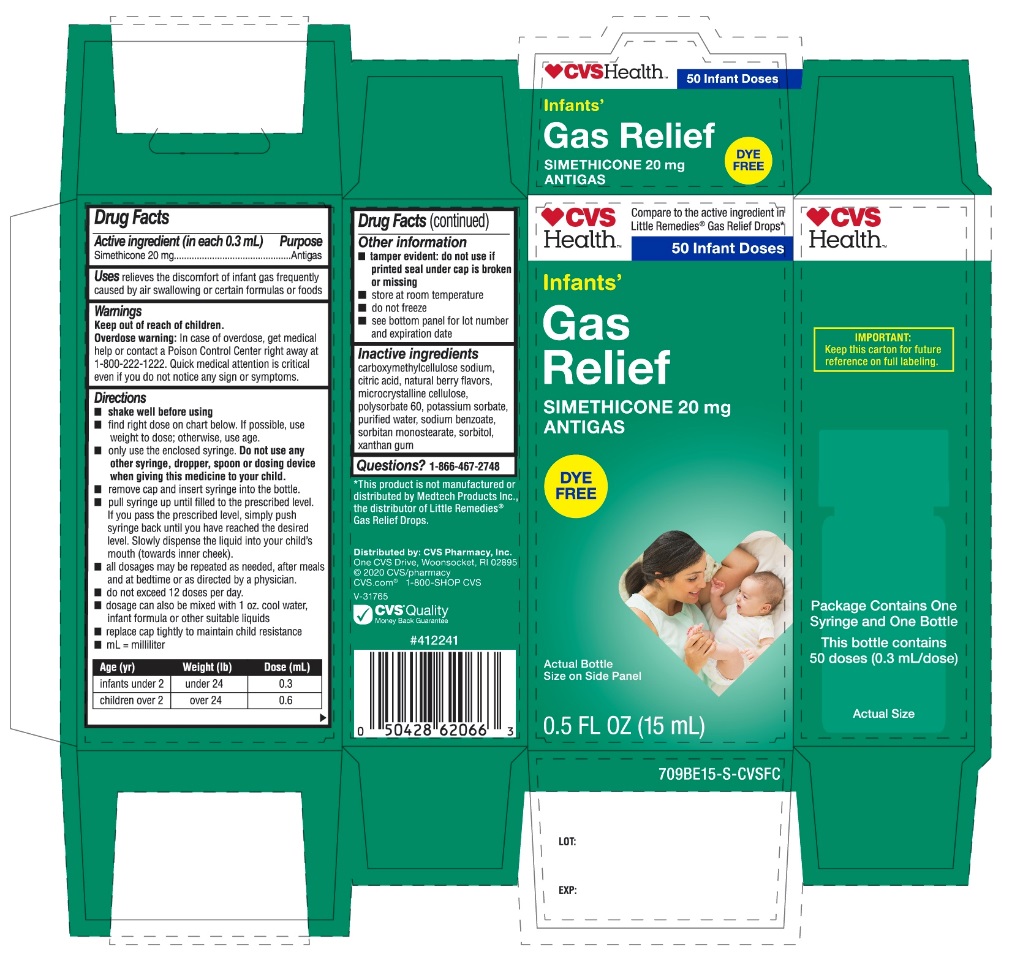 DRUG LABEL: CVS Health Infant

NDC: 69842-979 | Form: SUSPENSION/ DROPS
Manufacturer: CVS PHARMACY
Category: otc | Type: HUMAN OTC DRUG LABEL
Date: 20251209

ACTIVE INGREDIENTS: DIMETHICONE, UNSPECIFIED 20 mg/0.3 mL
INACTIVE INGREDIENTS: CARBOXYMETHYLCELLULOSE SODIUM, UNSPECIFIED; ANHYDROUS CITRIC ACID; MICROCRYSTALLINE CELLULOSE; POLYSORBATE 60; POTASSIUM SORBATE; WATER; SODIUM BENZOATE; SORBITAN MONOSTEARATE; SORBITOL; XANTHAN GUM

CVS Health™Gas Relief Simethicone Drops

Active ingredient (in each 0.3 mL)

Simethicone 20 mg

Purpose

Antigas

Uses

relieves the discomfort of infant gas frequently caused by air swallowing or certain formulas or foods

Directions

- shake well before using
- find right dose on chart below. If possible, use weight to dose; otherwise, use age.
- Only use the enclosed syringe. Do not use other syringe, dropper, spoon or dosing device when giving this medicine to your child.
- remove cap and insert syringe into the bottle.
- pull syringe up until filled to the prescribed level, if you passed the prescribed level, simply push syringe back until you have reached the desired level. Slowly dispense the liquid into your child’s mouth (towards inner cheek).
- all dosages may be repeated as needed, after meals and at bedtime or as directed by a physician.
- do not exceed 12 doses per day.
- dosage can also be mixed with 1 oz. cool water, infant formula or other suitable liquids.
- replace cap tightly to maintain child resistance
- mL = milliliter

Age (yr) | Weight (lb) | Dose (mL)
infants under 2 | under 24 | 0.3
children over 2 | over 24 | 0.6

Other information

- tamper evident: do not use if printed seal under cap is broken or missing
- Store at room temperature
- do not freeze
- see bottom panel for lot number and expiration date

Inactive ingredients

carboxymethylcellulose sodium, citric acid, natural berry flavors, microcrystalline cellulose, polysorbate 60, potassium sorbate, purified water, sodium benzoate, sorbitan monostearate, sorbitol, xanthan gum

Questions or comments?

1-866-467-2748

Principal Display Panel

CVSHealth™

Compare to the active ingredient in Little Remedies®Gas Relief*

50 Infant Doses

NDC# 69842-979.15

Gas Relief

SIMETHICONE 20 mg

ANTIGAS

DYE FREE

Actual Bottle size on Side Panel

0.5 FL OZ (15 mL)

*This product is not manufactured or distributed by Medtech Products Inc., the distributor of Little Remedies®Gas Relief Drops.

Distributed by: CVS Pharmacy, Inc.

One CVS Drive, Woonsocket, RI 02895

@ 2020 CVS/pharmacy CVS.com®

1-800-SHOP CVS

V-31765

CVS Quality

Money Back Guarantee

IMPORTANT: Keep this Carton for future reference on full labeling

Package Label 50 Infant Doses